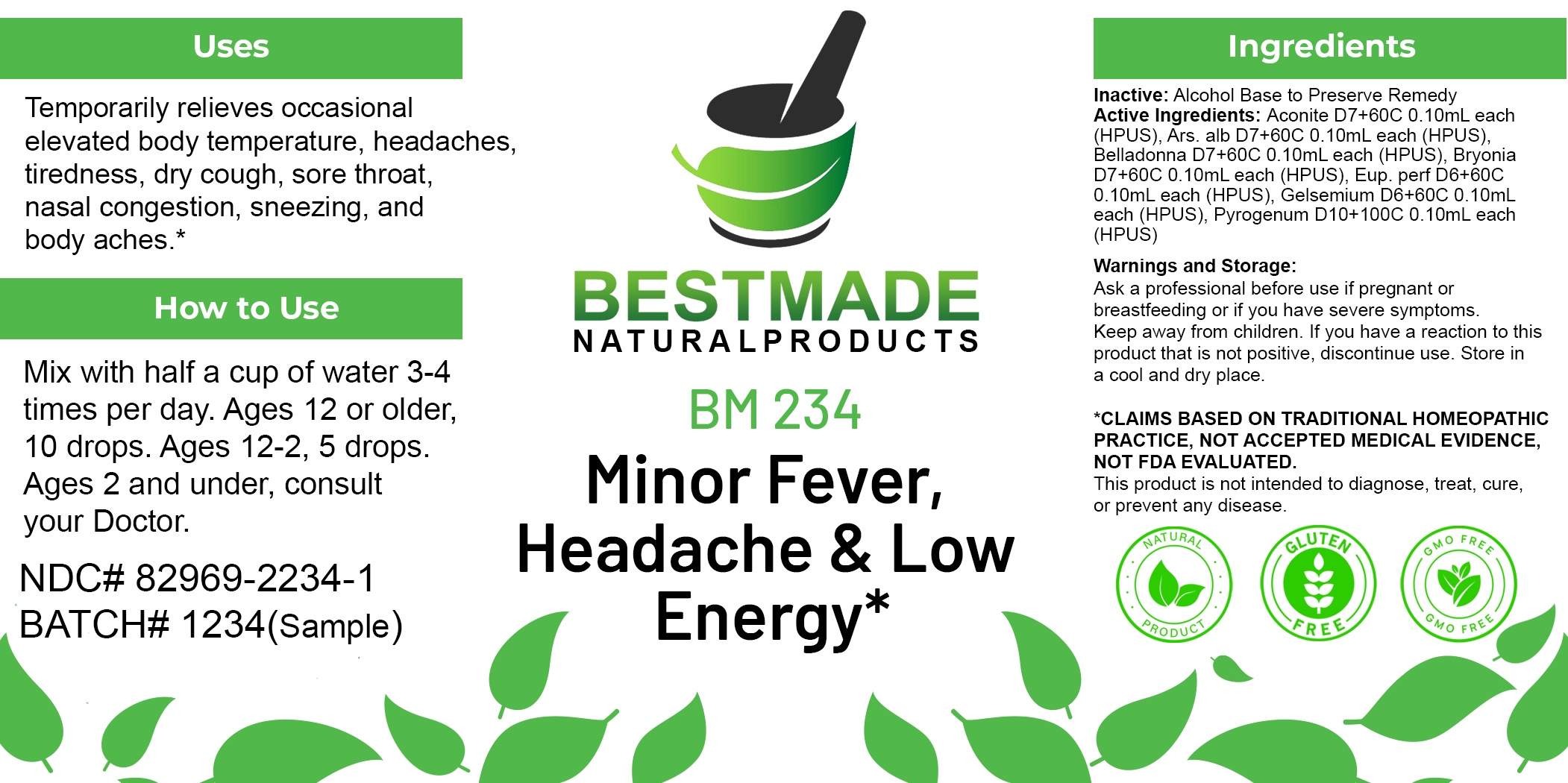 DRUG LABEL: Bestmade Natural Products BM234
NDC: 82969-2234 | Form: LIQUID
Manufacturer: Bestmade Natural Products
Category: homeopathic | Type: HUMAN OTC DRUG LABEL
Date: 20250304

ACTIVE INGREDIENTS: BRYONIA ALBA ROOT 30 [hp_C]/30 [hp_C]; ARSENIC TRIOXIDE 30 [hp_C]/30 [hp_C]; ATROPA BELLADONNA 30 [hp_C]/30 [hp_C]; RANCID BEEF 30 [hp_C]/30 [hp_C]; GELSEMIUM SEMPERVIRENS ROOT 30 [hp_C]/30 [hp_C]; EUPATORIUM PERFOLIATUM FLOWERING TOP 30 [hp_C]/30 [hp_C]; ACONITUM NAPELLUS 30 [hp_C]/30 [hp_C]
INACTIVE INGREDIENTS: ALCOHOL 30 [hp_C]/30 [hp_C]

BM234

DOSAGE AND ADMINISTRATION

How to Use

Mix with half a cup of water 3-4 times per day. Ages 12 or older, 10 drops. Ages 12-2, 5 drops. Ages 2 and under, consult your Doctor.

Inactive:

Alcohol Base to Preserve Product

ACTIVE INGREDIENT

Active Ingredients: Aconite D7+60C 0.10mL each (HPUS), Ars. alb D7+60C 0.10mL each (HPUS), Belladonna D7+60C 0.10mL each (HPUS), Bryonia D7+60C 0.10mL each (HPUS), Eup. perf D6+60C 0.10mL each (HPUS), Gelsemium D6+60C 0.10mL each (HPUS), Pyrogenum D10+100C 0.10mL each (HPUS)

KEEP OUT OF REACH OF CHILDREN

Warnings and Storage:

Ask a professional before use if pregnant or breastfeeding or if you have severe symptoms.

Keep away from children. If you have a reaction to this product that is not positive, discontinue use. Store in a cool and dry place

*CLAIMS BASED ON TRADITIONAL HOMEOPATHIC PRACTICE, NOT ACCEPTED MEDICAL EVIDENCE NOT FDA EVALUATED.
This product is not intended to diagnose, treat, cure, or prevent any disease.

Warnings and Storage:

Ask a professional before use if pregnant or breastfeeding or if you have severe symptoms.

Keep away from children. If you have a reaction to this product that is not positive, discontinue use. Store in a cool and dry place

*CLAIMS BASED ON TRADITIONAL HOMEOPATHIC PRACTICE, NOT ACCEPTED MEDICAL EVIDENCE NOT FDA EVALUATED.
This product is not intended to diagnose, treat, cure, or prevent any disease.

Uses
Temporarily relieves occasional elevated body temperature, headaches, tiredness, dry cough, sore throat, nasal congestion, sneezing, and body aches.*

Uses
Temporarily relieves occasional elevated body temperature, headaches, tiredness, dry cough, sore throat, nasal congestion, sneezing, and body aches.*

Entire package label